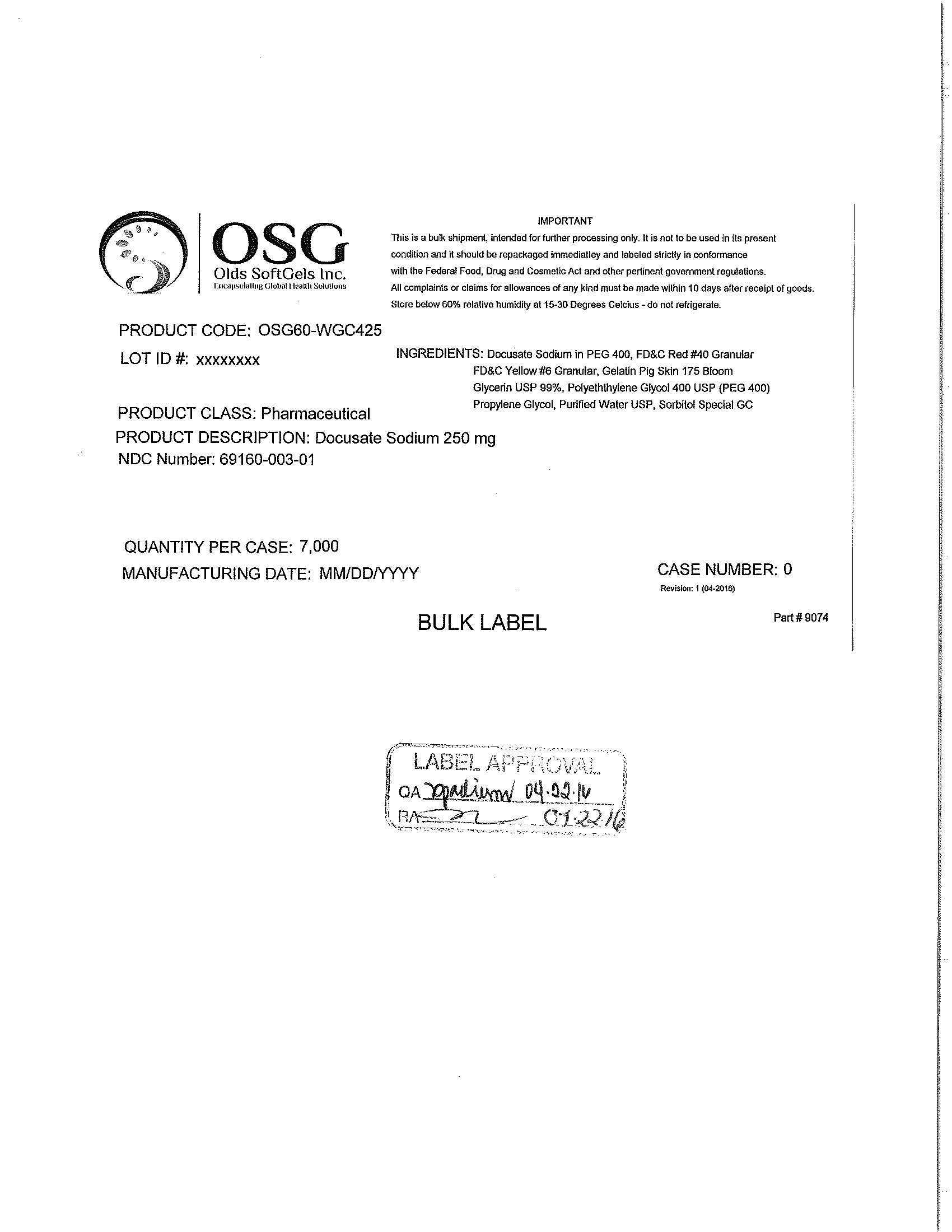 DRUG LABEL: Docusate Sodium 250mg
NDC: 69160-003 | Form: CAPSULE
Manufacturer: Olds Softgels Inc.
Category: otc | Type: HUMAN OTC DRUG LABEL
Date: 20200402

ACTIVE INGREDIENTS: DOCUSATE SODIUM 250 mg/1 1
INACTIVE INGREDIENTS: POLYETHYLENE GLYCOL 400; PROPYLENE GLYCOL; GELATIN; GLYCERIN; WATER; SORBITAN; SORBITOL; FD&C RED NO. 40; FD&C YELLOW NO. 6

ACTIVE INGREDIENT

Docusate Sodium 250 mg

PURPOSE

IMPORTANT

This is a bulk shipment, intended for further processing only. It is not to be used in its present condition and it should be repackaged immediately and labeled strictly in conformance with the Federal Food, Drug and Cosmetic Act and other pertinent government regulations.

Keep out of reach of children.

INDICATIONS AND USAGE

Olds SoftGels Inc

DOSAGE AND ADMINISTRATION

All complaints or claims for allowances of any kind must be made within 10 days after receipt of goods.

WARNINGS

All complaints or claims for allowances of any kind must be made within 10 days after receipt of goods.

INACTIVE INGREDIENTS

Red No. 40

Granular FD and C

Yellow No.6

Granular

Gelatin

Glycerin USP 99 Percent

Polyethylene

Glycol 400 USP PEG 400

Propylene glycol

Purified water

Sorbitol special GC

PACKAGE LABEL